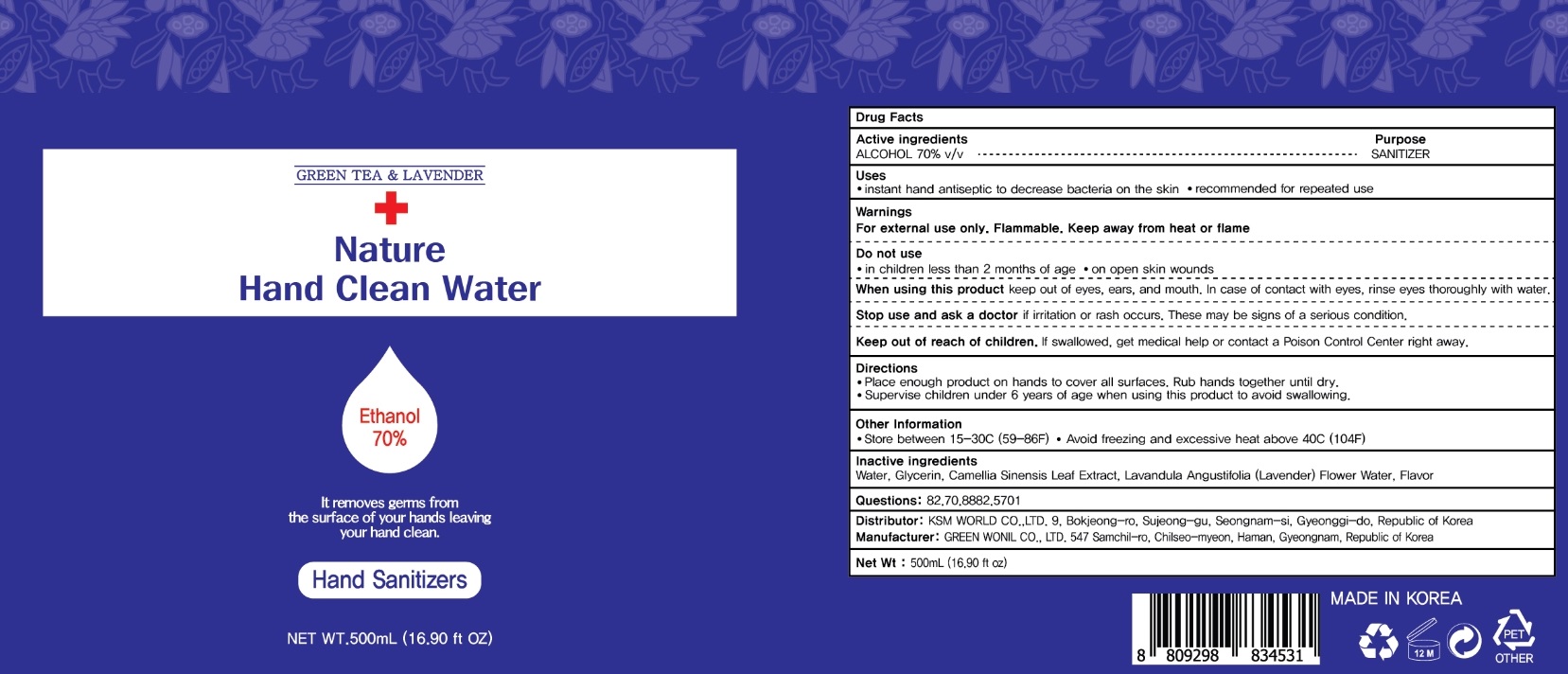 DRUG LABEL: Nature Hand Clean Water
NDC: 75577-020 | Form: GEL
Manufacturer: KSM WORLD CO.,LTD.
Category: otc | Type: HUMAN OTC DRUG LABEL
Date: 20200515

ACTIVE INGREDIENTS: ALCOHOL 350 mL/500 mL
INACTIVE INGREDIENTS: Water; Glycerin; GREEN TEA LEAF; LAVENDER OIL

ACTIVE INGREDIENT

ALCOHOL 70% v/v

INACTIVE INGREDIENTS

Water, Glycerin, Camellia Sinensis Leaf Extract, Lavandula Angustifolia (Lavender) Flower Water, Flavor

PURPOSE

Purpose: SANITIZER

WARNINGS

For external use only. Flammable. Keep away from heat or flame
--------------------------------------------------------------------------------------------------------
Do not use
• in children less than 2 months of age
• on open skin wounds
--------------------------------------------------------------------------------------------------------
When using this product keep out of eyes, ears, and mouth. In case of contact with eyes, rinse eyes thoroughly with water.
--------------------------------------------------------------------------------------------------------
Stop use and ask a doctor if irritation or rash occurs. These may be signs of a serious condition.

KEEP OUT OF REACH OF CHILDREN

If swallowed, get medical help or contact a Poison Control Center right away.

Uses

•instant hand antiseptic to decrease bacteria on the skin
•recommended for repeated use

Directions

• Place enough product on hands to cover all surfaces. Rub hands together until dry.
• Supervise children under 6 years of age when using this product to avoid swallowing.

Other Information

• Store between 15-30C (59-86F)
• Avoid freezing and excessive heat above 40C (104F)

Questions

82.70.8882.5701